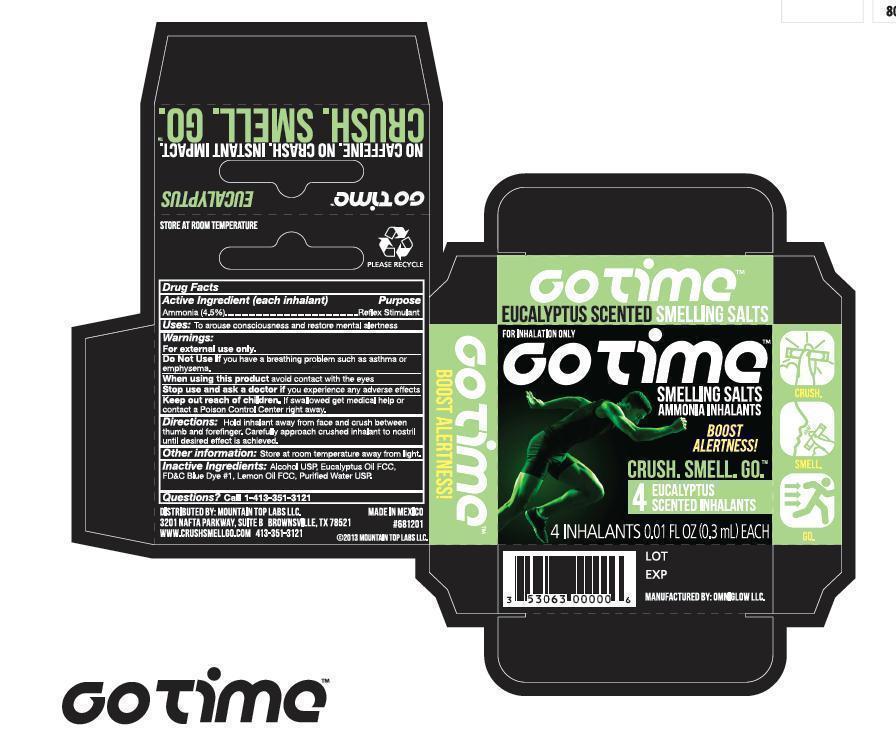 DRUG LABEL: GO TIME
NDC: 53063-1112 | Form: INHALANT
Manufacturer: Mountain Top Labs, LLC
Category: otc | Type: HUMAN OTC DRUG LABEL
Date: 20130313

ACTIVE INGREDIENTS: AMMONIA 0.013 mL/0.3 mL
INACTIVE INGREDIENTS: ALCOHOL; EUCALYPTUS OIL; FD&C BLUE NO. 1; LEMON OIL; WATER; ROSEMARY OIL

Drug Facts

Active ingredient (each inhalant)

Ammonia 4.5%

Purpose

Reflex Stimulant

Uses

To arouse consciousness and restore mental alertness.

Warnings

For external use only

Do not use if you have breathing problems such as asthma or emphysema.

When using this product avoid contact with the eyes.

Stop use and ask a doctor if you experience any adverse effects.

Keep out of reach of children. If swallowed, get medical help or contact a Poison Control Center right away.

Directions

Hold inhalant away from face and crush between thumb and forefinger. Carefully approach crushed inhalant to nostril until desired effect is achieved.

Other information

Store at room temperature away from light.

Inactive ingredients

Alcohol USP, Eucalyptus Oil, FD and C Blue Dye #1, Lemon Oil, Purified Water USP, Rosemary Oil

Questions?

Call 1-801-448-6809

PACKAGE LABEL

NDC 53063-1112-1